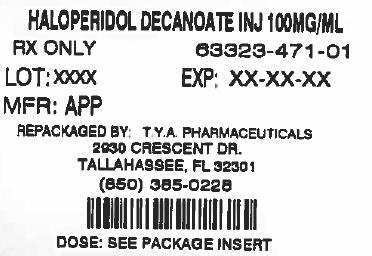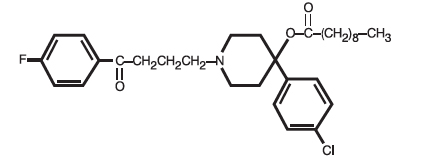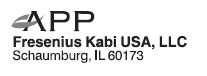 DRUG LABEL: Haloperidol Decanoate
NDC: 64725-0471 | Form: INJECTION
Manufacturer: TYA Pharmaceuticals
Category: prescription | Type: HUMAN PRESCRIPTION DRUG LABEL
Date: 20140731

ACTIVE INGREDIENTS: HALOPERIDOL DECANOATE 100 mg/1 mL
INACTIVE INGREDIENTS: SESAME OIL; BENZYL ALCOHOL

Haloperidol Decanoate Injection

For IM Injection Only

Rx only

WARNING

Increased Mortality in Elderly Patients with Dementia-Related Psychosis- Elderly patients with dementia-related psychosis treated with antipsychotic drugs are at an increased risk of death. Analyses of seventeen placebo-controlled trials (modal duration of 10 weeks), largely in patients taking atypical antipsychotic drugs, revealed a risk of death in drug-treated patients of between 1.6 to 1.7 times the risk of death in placebo-treated patients. Over the course of a typical 10-week controlled trial, the rate of death in drug-treated patients was about 4.5%, compared to a rate of about 2.6% in the placebo group. Although the causes of death were varied, most of the deaths appeared to be either cardiovascular (e.g., heart failure, sudden death) or infectious (e.g., pneumonia) in nature. Observational studies suggest that, similar to atypical antipsychotic drugs, treatment with conventional antipsychotic drugs may increase mortality. The extent to which the findings of increased mortality in observational studies may be attributed to the antipsychotic drug as opposed to some characteristic(s) of the patients is not clear. Haloperidol Decanoate Injection is not approved for the treatment of patients with dementia-related psychosis (see). WARNINGS

DESCRIPTION

Haloperidol decanoate is the decanoate ester of the butyrophenone, haloperidol. It has a markedly extended duration of effect. It is available as a colorless/pink to yellow amber solution in sesame oil in sterile form for intramuscular (IM) injection. The structural formula of haloperidol decanoate, 4-(4-chlorophenyl)-1-[4-(4-fluorophenyl)-4-oxobutyl]-4 piperidinyl decanoate, is:

C H CIFNO M.W. 530.1231413

Haloperidol decanoate is almost insoluble in water (0.01 mg/mL), but is soluble in most organic solvents.

Each mL of Haloperidol Decanoate Injection, 50 mg/mL, contains 50 mg haloperidol (present as haloperidol decanoate 70.52 mg) in a sesame oil vehicle, with 1.2% (w/v) benzyl alcohol as a preservative.

Each mL of Haloperidol Decanoate Injection, 100 mg/mL, contains 100 mg haloperidol (present as haloperidol decanoate 141.04 mg) in a sesame oil vehicle, with 1.2% (w/v) benzyl alcohol as a preservative.

CLINICAL PHARMACOLOGY

Haloperidol decanoate is the long-acting form of haloperidol. The basic effects of haloperidol decanoate are no different from those of haloperidol with the exception of duration of action. Haloperidol blocks the effects of dopamine and increases its turnover rate; however, the precise mechanism of action is unknown.

Administration of haloperidol decanoate in sesame oil results in slow and sustained release of haloperidol. The plasma concentrations of haloperidol gradually rise, reaching a peak at about 6 days after the injection, and falling thereafter, with an apparent half-life of about 3 weeks. Steady-state plasma concentrations are achieved after the third or fourth dose. The relationship between dose of haloperidol decanoate and plasma haloperidol concentration is roughly linear for doses below 450 mg. It should be noted, however, that the pharmacokinetics of haloperidol decanoate following intramuscular injections can be quite variable between subjects.

INDICATIONS AND USAGE

Haloperidol Decanoate Injection is indicated for the treatment of schizophrenic patients who require prolonged parenteral antipsychotic therapy.

CONTRAINDICATIONS

Since the pharmacologic and clinical actions of Haloperidol Decanoate Injection are attributed to haloperidol as the active medication, and additional information are those of haloperidol, modified only to reflect the prolonged action. , , CONTRAINDICATIONSWARNINGS

Haloperidol is contraindicated in severe toxic central nervous system depression or comatose states from any cause and in individuals who are hypersensitive to this drug or have Parkinson’s disease.

WARNINGS

Increased Mortality in Elderly Patients with Dementia-Related Psychosis

Elderly patients with dementia-related psychosis treated with antipsychotic drugs are at an increased risk of death. Haloperidol Decanoate Injection is not approved for the treatment of patients with dementia-related psychosis (see). BOXED WARNING

Cardiovascular Effects

Cases of sudden death, QT-prolongation, and Torsades de Pointes have been reported in patients receiving haloperidol. Higher than recommended doses of any formulation and intravenous administration of haloperidol appear to be associated with a higher risk of QT-prolongation and Torsades de Pointes. Although cases have been reported even in the absence of predisposing factors, particular caution is advised in treating patients with other QT-prolonging conditions (including electrolyte imbalance [particularly hypokalemia and hypomagnesemia], drugs known to prolong QT, underlying cardiac abnormalities, hypothyroidism, and familial long QT-syndrome). HALOPERIDOL INJECTION MUST NOT BE ADMINISTERED INTRAVENOUSLY. DECANOATE

Tardive Dyskinesia

A syndrome consisting of potentially irreversible, involuntary, dyskinetic movements may develop in patients treated with antipsychotic drugs. Although the prevalence of the syndrome appears to be highest among the elderly, especially elderly women, it is impossible to rely upon prevalence estimates to predict, at the inception of antipsychotic treatment, which patients are likely to develop the syndrome. Whether antipsychotic drug products differ in their potential to cause tardive dyskinesia is unknown.

Both the risk of developing tardive dyskinesia and the likelihood that it will become irreversible are believed to increase as the duration of treatment and the total cumulative dose of antipsychotic drugs administered to the patient increase. However, the syndrome can develop, although much less commonly, after relatively brief treatment periods at low doses.

There is no known treatment for established cases of tardive dyskinesia, although the syndrome may remit, partially or completely, if antipsychotic treatment is withdrawn. Antipsychotic treatment, itself, however, may suppress (or partially suppress) the signs and symptoms of the syndrome and thereby may possibly mask the underlying process. The effect that symptomatic suppression has upon the long-term course of the syndrome is unknown.

Given these considerations, antipsychotic drugs should be prescribed in a manner that is most likely to minimize the occurrence of tardive dyskinesia. Chronic antipsychotic treatment should generally be reserved for patients who suffer from a chronic illness that 1) is known to respond to antipsychotic drugs, and 2) for whom alternative, equally effective, but potentially less harmful treatments are available or appropriate. In patients who do require chronic treatment, the smallest dose and the shortest duration of treatment producing a satisfactory clinical response should be sought. The need for continued treatment should be reassessed periodically. not

If signs and symptoms of tardive dyskinesia appear in a patient on antipsychotics, drug discontinuation should be considered. However, some patients may require treatment despite the presence of the syndrome. (For further information about the description of tardive dyskinesia and its clinical detection, please refer to .) ADVERSE REACTIONS

Neuroleptic Malignant Syndrome (NMS)

A potentially fatal symptom complex sometimes referred to as Neuroleptic Malignant Syndrome (NMS) has been reported in association with antipsychotic drugs. Clinical manifestations of NMS are hyperpyrexia, muscle rigidity, altered mental status (including catatonic signs) and evidence of autonomic instability (irregular pulse or blood pressure, tachycardia, diaphoresis, and cardiac dysrhythmias). Additional signs may include elevated creatine phosphokinase, myoglobinuria (rhabdomyolysis) and acute renal failure.

The diagnostic evaluation of patients with this syndrome is complicated. In arriving at a diagnosis, it is important to identify cases where the clinical presentation includes both serious medical illness (e.g., pneumonia, systemic infection, etc.) and untreated or inadequately treated extrapyramidal signs and symptoms (EPS). Other important considerations in the differential diagnosis include central anticholinergic toxicity, heat stroke, drug fever and primary central nervous system (CNS) pathology.

The management of NMS should include 1) immediate discontinuation of antipsychotic drugs and other drugs not essential to concurrent therapy, 2) intensive symptomatic treatment and medical monitoring, and 3) treatment of any concomitant serious medical problems for which specific treatments are available. There is no general agreement about specific pharmacological treatment regimens for uncomplicated NMS.

If a patient requires antipsychotic drug treatment after recovery from NMS, the potential reintroduction of drug therapy should be carefully considered. The patient should be carefully monitored, since recurrences of NMS have been reported.

Hyperpyrexia and heat stroke, not associated with the above symptom complex, have also been reported with haloperidol.

Combined Use of Haloperidol and Lithium

An encephalopathic syndrome (characterized by weakness, lethargy, fever, tremulousness and confusion, extrapyramidal symptoms, leukocytosis, elevated serum enzymes, BUN, and fasting blood sugar) followed by irreversible brain damage has occurred in a few patients treated with lithium plus haloperidol. A causal relationship between these events and the concomitant administration of lithium and haloperidol has not been established; however, patients receiving such combined therapy should be monitored closely for early evidence of neurological toxicity and treatment discontinued promptly if such signs appear.

General

A number of cases of bronchopneumonia, some fatal, have followed the use of antipsychotic drugs, including haloperidol. It has been postulated that lethargy and decreased sensation of thirst due to central inhibition may lead to dehydration, hemoconcentration and reduced pulmonary ventilation. Therefore, if the above signs and symptoms appear, especially in the elderly, the physician should institute remedial therapy promptly.

Although not reported with haloperidol, decreased serum cholesterol and/or cutaneous and ocular changes have been reported in patients receiving chemically-related drugs.

PRECAUTIONS

Leukopenia, Neutropenia, and Agranulocytosis

In clinical trial and/or postmarketing experience, events of leukopenia/neutropenia have been reported temporally related to antipsychotic agents, including haloperidol. Agranulocytosis has also been reported. Class Effect:

Possible risk factors for leukopenia/neutropenia include pre-existing low white blood cell count (WBC) and history of drug-induced leukopenia/neutropenia. Patients with a history of a clinically significant low WBC or a drug-induced leukopenia/neutropenia should have their complete blood count (CBC) monitored frequently during the first few months of therapy and discontinuation of haloperidol decanoate should be considered at the first sign of a clinically significant decline in WBC in the absence of other causative factors.

Patients with clinically significant neutropenia should be carefully monitored for fever or other symptoms or signs of infection and treated promptly if such symptoms or signs occur. Patients with severe neutropenia (absolute neutrophil count <1000/mm) should discontinue haloperidol decanoate and have their WBC followed until recovery.^3

Other

Haloperidol decanoate should be administered cautiously to patients:

- with severe cardiovascular disorders, because of the possibility of transient hypotension and/or precipitation of anginal pain. Should hypotension occur and a vasopressor be required, epinephrine should not be used since haloperidol may block its vasopressor activity, and paradoxical further lowering of the blood pressure may occur. Instead, metaraminol, phenylephrine or norepinephrine should be used.
- receiving anticonvulsant medications, with a history of seizures, or with EEG abnormalities, because haloperidol may lower the convulsive threshold. If indicated, adequate anticonvulsant therapy should be concomitantly maintained.
- with known allergies, or with a history of allergic reactions to drugs.
- receiving anticoagulants, since an isolated instance of interference occurred with the effects of one anticoagulant (phenindione).

If concomitant antiparkinson medication is required, it may have to be continued after haloperidol decanoate is discontinued because of the prolonged action of haloperidol decanoate. If both drugs are discontinued simultaneously, extrapyramidal symptoms may occur. The physician should keep in mind the possible increase in intraocular pressure when anticholinergic drugs, including antiparkinson agents, are administered concomitantly with haloperidol decanoate.

When haloperidol decanoate is used to control mania in cyclic disorders, there may be a rapid mood swing to depression.

Severe neurotoxicity (rigidity, inability to walk or talk) may occur in patients with thyrotoxicosis who are also receiving antipsychotic medication, including haloperidol.

Information for Patients

Haloperidol decanoate may impair the mental and/or physical abilities required for the performance of hazardous tasks such as operating machinery or driving a motor vehicle. The ambulatory patient should be warned accordingly.

The use of alcohol with this drug should be avoided due to possible additive effects and hypotension.

Drug Interactions

Drug-drug interactions can be pharmacodynamic (combined pharmacologic effects) or pharmacokinetic (alteration of plasma levels). The risks of using haloperidol in combination with other drugs have been evaluated as described below.

Pharmacodynamic Interactions

Since QT-prolongation has been observed during haloperidol treatment, caution is advised when prescribing to patient with QT-prolongation conditions (long QT-syndrome, hypokalemia, electrolyte imbalance) or to patients receiving medications known to prolong the QT-interval or known to cause electrolyte imbalance.

As with other antipsychotic agents, it should be noted that haloperidol may be capable of potentiating CNS depressants such as anesthetics, opiates and alcohol.

Ketoconazole is a potent inhibitor of CYP3A4. Increases in QTc have been observed when haloperidol was given in combination with the metabolic inhibitors ketoconazole (400 mg/day) and paroxetine (20 mg/day). It may be necessary to reduce the haloperidol dosage.

Pharmacokinetic Interactions

The Effect of Other Drugs on Haloperidol Decanoate

Haloperidol is metabolized by several routes, including the glucuronidation and the cytochrome P450 enzyme system. Inhibition of these routes of metabolism by another drug may result in increased haloperidol concentrations and potentially increase the risk of certain adverse events, including QT-prolongation.

Drugs Characterized as Substrates, Inhibitors or Inducers of CYP3A4, CYP2D6 or Glucuronidation

In pharmacokinetic studies, mild to moderately increased haloperidol concentrations have been reported when haloperidol was given concomitantly with drugs characterized as substrates or inhibitors of CYP3A4 or CYP2D6 isoenzymes, such as, itraconazole, nefazodone, buspirone, venlafaxine, alprazolam, fluvoxamine, quinidine, fluoxetine, sertraline, chlorpromazine, and promethazine.

When prolonged treatment (1 to 2 weeks) with enzyme-inducing drugs such as rifampin or carbamazepine is added to haloperidol therapy, this results in a significant reduction of haloperidol plasma levels.

Rifampin

In a study of 12 schizophrenic patients coadministered oral haloperidol and rifampin, plasma haloperidol levels were decreased by a mean of 70% and mean scores on the Brief Psychiatric Rating Scale were increased from baseline. In 5 other schizophrenic patients treated with oral haloperidol and rifampin, discontinuation of rifampin produced a mean 3.3-fold increase in haloperidol concentrations.

Carbamazepine

In a study in 11 schizophrenic patients co-administered haloperidol and increasing doses of carbamazepine, haloperidol plasma concentrations decreased linearly with increasing carbamazepine concentrations.

Thus, careful monitoring of clinical status is warranted when enzyme inducing drugs such as rifampin or carbamazepine are administered or discontinued in haloperidol-treated patients. During combination treatment, the haloperidol dose should be adjusted, when necessary. After discontinuation of such drugs, it may be necessary to reduce the dosage of haloperidol.

Valproate

Sodium valproate, a drug known to inhibit glucuronidation, does not affect haloperidol plasma concentrations.

Carcinogenesis, Mutagenesis, Impairment of Fertility

No mutagenic potential of haloperidol decanoate was found in the Ames Salmonella microsomal activation assay. Negative or inconsistent positive findings have been obtained in and studies of effects of short-acting haloperidol on chromosome structure and number. The available cytogenetic evidence is considered too inconsistent to be conclusive at this time. in vitroin vivo

Carcinogenicity studies using oral haloperidol were conducted in Wistar rats (dosed at up to 5 mg/kg daily for 24 months) and in Albino Swiss mice (dosed at up to 5 mg/kg daily for 18 months). In the rat study survival was less than optimal in all dose groups, reducing the number of rats at risk for developing tumors. However, although a relatively greater number of rats survived to the end of the study in high-dose male and female groups, these animals did not have a greater incidence of tumors than control animals. Therefore, although not optimal, this study does suggest the absence of a haloperidol-related increase in the incidence of neoplasia in rats at doses up to 20 times the usual daily human dose for chronic or resistant patients.

In female mice at 5 and 20 times the highest initial daily dose for chronic or resistant patients, there was a statistically significant increase in mammary gland neoplasia and total tumor incidence; at 20 times the same daily dose there was a statistically significant increase in pituitary gland neoplasia. In male mice, no statistically significant differences in incidences of total tumors or specific tumor types were noted.

Antipsychotic drugs elevate prolactin levels; the elevation persists during chronic administration. Tissue culture experiments indicate that approximately one-third of human breast cancers are prolactin dependent , a factor of potential importance if the prescription of these drugs is contemplated in a patient with a previously detected breast cancer. Although disturbances such as galactorrhea, amenorrhea, gynecomastia, and impotence have been reported, the clinical significance of elevated serum prolactin levels is unknown for most patients. in vitro

An increase in mammary neoplasms has been found in rodents after chronic administration of antipsychotic drugs. Neither clinical studies nor epidemiologic studies conducted to date, however, have shown an association between chronic administration of these drugs and mammary tumorigenesis; the available evidence is considered too limited to be conclusive at this time.

Usage in Pregnancy

Pregnancy Category C

Rodents given up to 3 times the usual maximum human dose of haloperidol decanoate showed an increase in incidence of resorption, fetal mortality, and pup mortality. No fetal abnormalities were observed.

Cleft palate has been observed in mice given oral haloperidol at 15 times the usual maximum human dose. Cleft palate in mice appears to be a non-specific response to stress or nutritional imbalance as well as to a variety of drugs, and there is no evidence to relate this phenomenon to predictable human risk for most of these agents.

There are no adequate and well-controlled studies in pregnant women. There are reports, however, of cases of limb malformations observed following maternal use of haloperidol along with other drugs which have suspected teratogenic potential during the first trimester of pregnancy. Causal relationships were not established with these cases. Since such experience does not exclude the possibility of fetal damage due to haloperidol, haloperidol decanoate should be used during pregnancy or in women likely to become pregnant only if the benefit clearly justifies a potential risk to the fetus.

Non-teratogenic Effects

Neonates exposed to antipsychotic drugs (including haloperidol) during the third trimester of pregnancy are at risk for extrapyramidal and/or withdrawal symptoms following delivery. There have been reports of agitation, hypertonia, hypotonia, tremor, somnolence, respiratory distress, and feeding disorder in these neonates. These complications have varied in severity; while in some cases symptoms have been self-limited, in other cases neonates have required intensive care unit support and prolonged hospitalization.

Haloperidol decanoate should be used during pregnancy only if the potential benefit justifies the potential risk to the fetus.

Nursing Mothers

Since haloperidol is excreted in human breast milk, infants should not be nursed during drug treatment with haloperidol decanoate.

Pediatric Use

Safety and effectiveness of haloperidol decanoate in children have not been established.

Geriatric Use

Clinical studies of haloperidol did not include sufficient numbers of subjects aged 65 and over to determine whether they respond differently from younger subjects. Other reported clinical experience has not consistently identified differences in responses between the elderly and younger patients. However, the prevalence of tardive dyskinesia appears to be highest among the elderly, especially elderly women (see). Also, the pharmacokinetics of haloperidol in geriatric patients generally warrants the use of lower doses (see). WARNINGS, Tardive Dyskinesia DOSAGE AND ADMINISTRATION

ADVERSE REACTIONS

Adverse reactions following the administration of Haloperidol Decanoate Injection are those of haloperidol. Since vast experience has accumulated with haloperidol, the adverse reactions are reported for that compound as well as for haloperidol decanoate. As with all injectable medications, local tissue reactions have been reported with haloperidol decanoate.

Cardiovascular Effects

Tachycardia, hypotension, and hypertension have been reported. QT-prolongation and/or ventricular arrhythmias have also been reported, in addition to ECG pattern changes compatible with the polymorphous configuration of Torsades de Pointes, and may occur more frequently with high doses and in predisposed patients (see and). WARNINGSPRECAUTIONS

Cases of sudden and unexpected death have been reported in association with the administration of Haloperidol Decanoate Injection. The nature of the evidence makes it impossible to determine definitively what role, if any, Haloperidol Decanoate Injection played in the outcome of the reported cases. The possibility that Haloperidol Decanoate Injection caused death cannot, of course, be excluded, but it is to be kept in mind that sudden and unexpected death may occur in psychotic patients when they go untreated or when they are treated with other antipsychotic drugs.

CNS Effects

Extrapyramidal Symptoms (EPS)

EPS during the administration of haloperidol have been reported frequently, often during the first few days of treatment. EPS can be categorized generally as Parkinson-like symptoms, akathisia, or dystonia (including opisthotonos and oculogyric crisis). While all can occur at relatively low doses, they occur more frequently and with greater severity at higher doses. The symptoms may be controlled with dose reductions or administration of antiparkinson drugs such as benztropine mesylate USP or trihexyphenidyl hydrochloride USP. It should be noted that persistent EPS have been reported; the drug may have to be discontinued in such cases.

Dystonia

Symptoms of dystonia, prolonged abnormal contractions of muscle groups, may occur in susceptible individuals during the first few days of treatment. Dystonic symptoms include: spasm of the neck muscles, sometimes progressing to tightness of the throat, swallowing difficulty, difficulty breathing, and/or protrusion of the tongue. While these symptoms can occur at low doses, they occur more frequently and with greater severity with high potency and at higher doses of first generation antipsychotic drugs. An elevated risk of acute dystonia is observed in males and younger age groups. Class Effect:

Withdrawal Emergent Neurological Signs

Generally, patients receiving short-term therapy experience no problems with abrupt discontinuation of antipsychotic drugs. However, some patients on maintenance treatment experience transient dyskinetic signs after abrupt withdrawal. In certain of these cases the dyskinetic movements are indistinguishable from the syndrome described below under except for duration. Although the long-acting properties of haloperidol decanoate provide gradual withdrawal, it is not known whether gradual withdrawal of antipsychotic drugs will reduce the rate of occurrence of withdrawal emergent neurological signs. “Tardive Dyskinesia”

Tardive Dyskinesia

As with all antipsychotic agents haloperidol has been associated with persistent dyskinesias. Tardive dyskinesia, a syndrome consisting of potentially irreversible, involuntary, dyskinetic movements, may appear in some patients on long-term therapy with haloperidol decanoate or may occur after drug therapy has been discontinued. The risk appears to be greater in elderly patients on high-dose therapy, especially females. The symptoms are persistent and in some patients appear irreversible. The syndrome is characterized by rhythmical involuntary movements of tongue, face, mouth, or jaw (e.g., protrusion of tongue, puffing of cheeks, puckering of mouth, chewing movements). Sometimes these may be accompanied by involuntary movements of extremities and the trunk.

There is no known effective treatment for tardive dyskinesia; antiparkinson agents usually do not alleviate the symptoms of this syndrome. It is suggested that all antipsychotic agents be discontinued if these symptoms appear. Should it be necessary to reinstitute treatment, or increase the dosage of the agent, or switch to a different antipsychotic agent, this syndrome may be masked.

It has been reported that fine vermicular movement of the tongue may be an early sign of tardive dyskinesia and if the medication is stopped at that time the full syndrome may not develop.

Tardive Dystonia

Tardive dystonia, not associated with the above syndrome, has also been reported. Tardive dystonia is characterized by delayed onset of choreic or dystonic movements, is often persistent, and has the potential of becoming irreversible.

Other CNS Effects

Insomnia, restlessness, anxiety, euphoria, agitation, drowsiness, depression, lethargy, headache, confusion, vertigo, grand mal seizures, exacerbation of psychotic symptoms including hallucinations, and catatonic-like behavioral states which may be responsive to drug withdrawal and/or treatment with anticholinergic drugs.

Body as a Whole

Neuroleptic malignant syndrome (NMS), hyperpyrexia and heat stroke have been reported with haloperidol (see for further information concerning NMS). WARNINGS

Hematologic Effects

Reports have appeared citing the occurrence of mild and usually transient leukopenia and leukocytosis, minimal decreases in red blood cell counts, anemia, or a tendency toward lymphomonocytosis. Agranulocytosis has rarely been reported to have occurred with the use of haloperidol, and then only in association with other medication (see). PRECAUTIONS, Leukopenia, Neutropenia, and Agranulocytosis

Liver Effects

Impaired liver function and/or jaundice have been reported.

Dermatologic Reactions

Maculopapular and acneiform skin reactions and isolated cases of photosensitivity and loss of hair.

Endocrine Disorders

Lactation, breast engorgement, mastalgia, menstrual irregularities, gynecomastia, impotence, increased libido, hyperglycemia, hypoglycemia and hyponatremia.

Gastrointestinal Effects

Anorexia, constipation, diarrhea, hypersalivation, dyspepsia, nausea and vomiting.

Autonomic Reactions

Dry mouth, blurred vision, urinary retention, diaphoresis and priapism.

Respiratory Effects

Laryngospasm, bronchospasm and increased depth of respiration.

Special Senses

Cataracts, retinopathy and visual disturbances.

Postmarketing Events

Hyperammonemia has been reported in a 5½ year old child with citrullinemia, an inherited disorder of ammonia excretion, following treatment with haloperidol.

OVERDOSAGE

While overdosage is less likely to occur with a parenteral than with an oral medication, information pertaining to haloperidol is presented, modified only to reflect the extended duration of action of haloperidol decanoate.

Manifestations

In general, the symptoms of overdosage would be an exaggeration of known pharmacologic effects and adverse reactions, the most prominent of which would be: 1) severe extrapyramidal reactions, 2) hypotension, or 3) sedation. The patient would appear comatose with respiratory depression and hypotension which could be severe enough to produce a shock-like state. The extrapyramidal reactions would be manifested by muscular weakness or rigidity and a generalized or localized tremor, as demonstrated by the akinetic or agitans types, respectively. With accidental overdosage, hypertension rather than hypotension occurred in a two-year old child. The risk of ECG changes associated with Torsades de Pointes should be considered.

(For further information regarding Torsades de Pointes, please refer to .) ADVERSE REACTIONS

Treatment

Since there is no specific antidote, treatment is primarily supportive. A patent airway must be established by use of an oropharyngeal airway or endotracheal tube or, in prolonged cases of coma, by tracheostomy. Respiratory depression may be counteracted by artificial respiration and mechanical respirators. Hypotension and circulatory collapse may be counteracted by use of intravenous fluids, plasma, or concentrated albumin, and vasopressor agents such as metaraminol, phenylephrine and norepinephrine. Epinephrine should not be used. In case of severe extrapyramidal reactions, antiparkinson medication should be administered, and should be continued for several weeks, and then withdrawn gradually as extrapyramidal symptoms may emerge. ECG and vital signs should be monitored especially for signs of QT-prolongation or dysrhythmias and monitoring should continue until the ECG is normal. Severe arrhythmias should be treated with appropriate anti-arrhythmic measures.

DOSAGE AND ADMINISTRATION

Haloperidol Decanoate Injection should be administered by deep intramuscular injection. A 21 gauge needle is recommended. The maximum volume per injection site should not exceed 3 mL. DO NOT ADMINISTER INTRAVENOUSLY.

Parenteral drug products should be inspected visually for particulate matter and discoloration prior to administration, whenever solution and container permit.

Haloperidol Decanoate Injection is intended for use in schizophrenic patients who require prolonged parenteral antipsychotic therapy. These patients should be previously stabilized on antipsychotic medication before considering a conversion to haloperidol decanoate. Furthermore, it is recommended that patients being considered for haloperidol decanoate therapy have been treated with, and tolerate well, short-acting haloperidol in order to reduce the possibility of an unexpected adverse sensitivity to haloperidol. Close clinical supervision is required during the initial period of dose adjustment in order to minimize the risk of overdosage or reappearance of psychotic symptoms before the next injection. During dose adjustment or episodes of exacerbation of symptoms of schizophrenia, haloperidol decanoate therapy can be supplemented with short-acting forms of haloperidol.

The dose of haloperidol decanoate should be expressed in terms of its haloperidol content. The starting dose of haloperidol decanoate should be based on the patient’s age, clinical history, physical condition, and response to previous antipsychotic therapy. The preferred approach to determining the minimum effective dose is to begin with lower initial doses and to adjust the dose upward as needed. For patients previously maintained on low doses of antipsychotics (e.g., up to the equivalent of 10 mg/day oral haloperidol), it is recommended that the initial dose of haloperidol decanoate be 10 to 15 times the previous daily dose in oral haloperidol equivalents; limited clinical experience suggests that lower initial doses may be adequate.

Initial Therapy

Conversion from oral haloperidol to haloperidol decanoate can be achieved by using an initial dose of haloperidol decanoate that is 10 to 20 times the previous daily dose in oral haloperidol equivalents.

In patients who are elderly, debilitated, or stable on low doses of oral haloperidol (e.g., up to the equivalent of 10 mg/day oral haloperidol), a range of 10 to 15 times the previous daily dose in oral haloperidol equivalents is appropriate for initial conversion.

In patients previously maintained on higher doses of antipsychotics for whom a low dose approach risks recurrence of psychiatric decompensation and in patients whose long-term use of haloperidol has resulted in a tolerance to the drug, 20 times the previous daily dose in oral haloperidol equivalents should be considered for initial conversion, with downward titration on succeeding injections.

The initial dose of haloperidol decanoate should not exceed 100 mg regardless of previous antipsychotic dose requirements. If, therefore, conversion requires more than 100 mg of haloperidol decanoate as an initial dose, that dose should be administered in two injections, i.e., a maximum of 100 mg initially followed by the balance in 3 to 7 days.

Maintenance Therapy

The maintenance dosage of haloperidol decanoate must be individualized with titration upward or downward based on therapeutic response. The usual maintenance range is 10 to 15 times the previous daily dose in oral haloperidol equivalents dependent on the clinical response of the patient.

HALOPERIDOL DECANOATE DOSING RECOMMENDATIONS

Patients | Monthly; 1 Monthst | Maintenance
Stabilized on low daily oral doses (up to 10 mg/day) | 10 to 15 x Daily; Oral Dose | 10 to 15 x Previous Daily; Oral Dose
Elderly or Debilitated
High dose | 20 x Daily; Oral Dose | 10 to 15 x Previous Daily; Oral Dose
Risk of relapse
Tolerant to oral haloperidol

Close clinical supervision is required during initiation and stabilization of haloperidol decanoate therapy. Haloperidol decanoate is usually administered monthly or every 4 weeks. However, variation in patient response may dictate a need for adjustment of the dosing interval as well as the dose (see). CLINICAL PHARMACOLOGY

Clinical experience with haloperidol decanoate at doses greater than 450 mg per month has been limited.

HOW SUPPLIED

NDC:64725-0471-1 in a CARTON of 1 INJECTIONS

45803I

Revised: October 2012